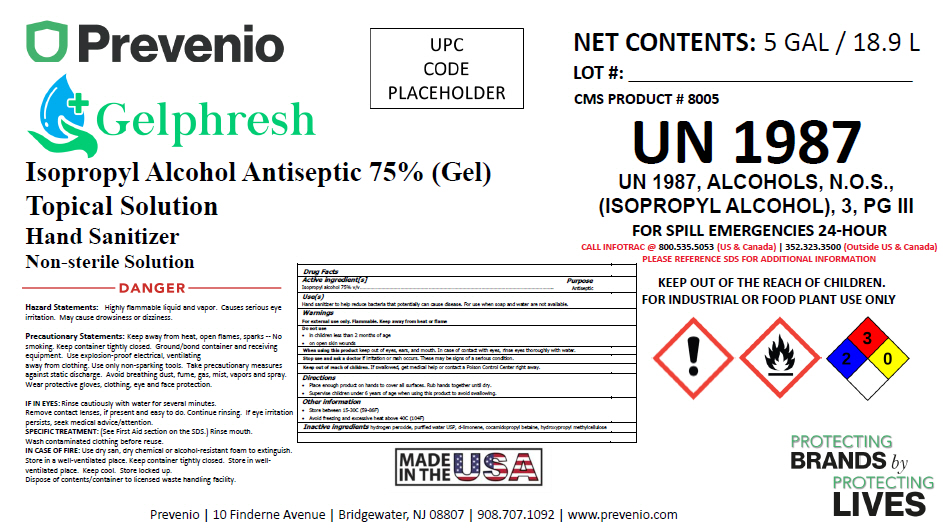 DRUG LABEL: GelpHresh
NDC: 54555-130 | Form: LIQUID
Manufacturer: Brainerd Chemical Company Inc.,
Category: otc | Type: HUMAN OTC DRUG LABEL
Date: 20200610

ACTIVE INGREDIENTS: alcohol 750 mL/1 L
INACTIVE INGREDIENTS: Cocamidopropyl Betaine; hydrogen peroxide; water; LIMONENE OXIDE, TRANS-(+)-; HYDROXYMETHYL CELLULOSE

GelpHresh

Drug Facts

Active ingredient[s]

Isopropyl alcohol 75% v/v

Purpose

Antiseptic

Use(s)

Hand sanitizer to help reduce bacteria that potentially can cause disease. For use when soap and water are not available.

Warnings

For external use only. Flammable. Keep away from heat or flame

Do not use

- in children less than 2 months of age
- on open skin wounds

When using this product keep out of eyes, ears, and mouth. In case of contact with eyes, rinse eyes thoroughly with water.

Stop use and ask a doctor if irritation or rash occurs. These may be signs of a serious condition.

Keep out of reach of children. If swallowed, get medical help or contact a Poison Control Center right away.

Directions

- Place enough product on hands to cover all surfaces. Rub hands together until dry.
- Supervise children under 6 years of age when using this product to avoid swallowing.

Other information

- Store between 15-30C (59-86F)
- Avoid freezing and excessive heat above 40C (104F)

Inactive ingredients

hydrogen peroxide, purified water USP, d-limonene, cocamidopropyl betaine, hydroxypropyl methylcellulose

PRINCIPAL DISPLAY PANEL - 18.9 L Jug Label

Prevenio

Gelphresh

Isopropyl Alcohol Antiseptic 75% (Gel)
Topical Solution
Hand Sanitizer
Non-sterile Solution

DANGER

Hazard Statements: Highly flammable liquid and vapor. Causes serious eye
irritation. May cause drowsiness or dizziness.

Precautionary Statements: Keep away from heat, open flames, sparks -- No
smoking. Keep container tightly closed. Ground/bond container and receiving
equipment. Use explosion-proof electrical, ventilating
away from clothing. Use only non-sparking tools. Take precautionary measures
against static discharge. Avoid breathing dust, fume, gas, mist, vapors and spray.
Wear protective gloves, clothing, eye and face protection.

IF IN EYES: Rinse cautiously with water for several minutes.
Remove contact lenses, if present and easy to do. Continue rinsing. If eye irritation
persists, seek medical advice/attention.
SPECIFIC TREATMENT: (See First Aid section on the SDS.) Rinse mouth.
Wash contaminated clothing before reuse.
IN CASE OF FIRE: Use dry san, dry chemical or alcohol-resistant foam to extinguish.
Store in a well-ventilated place. Keep container tightly closed. Store in well-
ventilated place. Keep cool. Store locked up.
Dispose of contents/container to licensed waste handling facility.

UPC
CODE
PLACEHOLDER

MADE
IN THE
USA

NET CONTENTS: 5 GAL / 18.9 L

LOT #: _____________________

CMS PRODUCT # 8005

UN 1987

UN 1987, ALCOHOLS, N.O.S.,
(ISOPROPYL ALCOHOL), 3, PG III

FOR SPILL EMERGENCIES 24-HOUR

CALL INFOTRAC @ 800.535.5053 (US & Canada) | 352.323.3500 (Outside US & Canada)
PLEASE REFERENCE SDS FOR ADDITIONAL INFORMATION

KEEP OUT OF THE REACH OF CHILDREN.
FOR INDUSTRIAL OR FOOD PLANT USE ONLY

PROTECTING
BRANDS by
PROTECTING
LIVES

Prevenio | 10 Finderne Avenue | Bridgewater, NJ 08807 | 908.707.1092 | www.prevenio.com